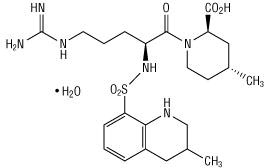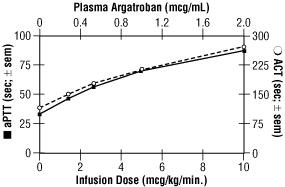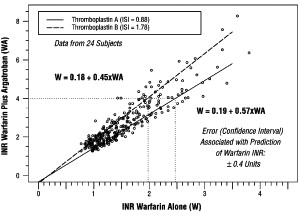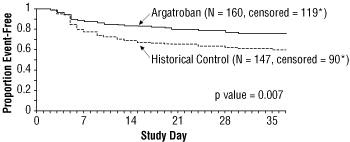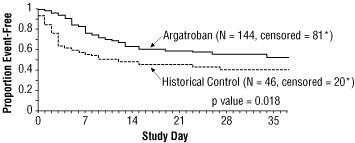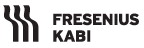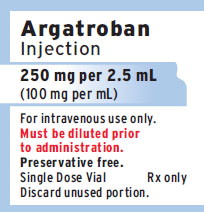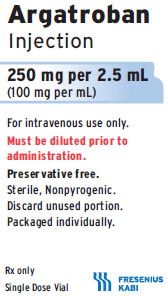 DRUG LABEL: Argatroban
NDC: 63323-526 | Form: INJECTION, SOLUTION
Manufacturer: Fresenius Kabi USA, LLC
Category: prescription | Type: HUMAN PRESCRIPTION DRUG LABEL
Date: 20251127

ACTIVE INGREDIENTS: ARGATROBAN 100 mg/1 mL
INACTIVE INGREDIENTS: PROPYLENE GLYCOL 954 mg/1 mL

HIGHLIGHTS OF PRESCRIBING INFORMATION

These highlights do not include all the information needed to use ARGATROBAN INJECTION safely and effectively. See full prescribing information for ARGATROBAN INJECTION.
ARGATROBAN INJECTION, for intravenous use
Initial U.S. Approval: 2000

RECENT MAJOR CHANGES

Dosage and Administration, Dosing in Pediatric Patients with Heparin Induced
Thrombocytopenia-Heparin Induced Thrombocytopenia and Thrombosis
Syndrome (2.5) Removed 1/2018

1 INDICATIONS AND USAGE

Argatroban is a direct thrombin inhibitor indicated:

- For prophylaxis or treatment of thrombosis in adult patients with heparin-induced thrombocytopenia (HIT) (1.1).
- As an anticoagulant in adult patients with or at risk for HIT undergoing percutaneous coronary intervention (PCI) (1.2).

2 DOSAGE AND ADMINISTRATION

Argatroban injection must be diluted 100-fold by mixing with 0.9% Sodium Chloride Injection, 5% Dextrose Injection or Lactated Ringer’s Injection to a final concentration of 1 mg/mL prior to administration (2.1).
Heparin-Induced Thrombocytopenia

The dose for heparin-induced thrombocytopenia without hepatic impairment is 2 mcg/kg/min administered as a continuous infusion (2.1).

Percutaneous Coronary Intervention

The dose for patients with or at risk for heparin-induced thrombocytopenia undergoing percutaneous coronary intervention is started at 25 mcg/kg/min and a bolus of 350 mcg/kg administered via a large bore intravenous line over 3 to 5 minutes (2.2).

3 DOSAGE FORMS AND STRENGTHS

Injection: 250 mg per 2.5 mL (100 mg per mL) clear solution in a single-dose vial (3).

4 CONTRAINDICATIONS

- Major bleeding (4).
- History of hypersensitivity to this product (4).

5 WARNINGS AND PRECAUTIONS

- Risk of hemorrhage: Hemorrhage at any site can occur (unexplained fall in hematocrit or blood pressure or other unexplained symptom may indicate hemorrhage.) Use with caution in patients at risk, including those receiving antiplatelet agents, thrombolytics, or other anticoagulants. (5.1).
- Use in hepatic impairment: Adjust starting dose and titrate carefully in patients with HIT who have moderate or severe hepatic impairment. Avoid use in PCI in patients with clinically significant hepatic impairment (5.2).

6 ADVERSE REACTIONS

- HIT patients: The most common (> 5%) adverse reactions were dyspnea, hypotension, fever, diarrhea, sepsis, and cardiac arrest (6.1).
- PCI patients: The most common (> 5%) adverse reactions were chest pain, hypotension, back pain, nausea, vomiting and headache (6.2).

To report SUSPECTED ADVERSE REACTIONS, contact Fresenius Kabi USA, LLC at 1-800-551-7176 or FDA at 1-800-FDA-1088 or www.fda.gov/medwatch.

7 DRUG INTERACTIONS

- Heparin: Allow sufficient time for heparin’s effect on aPTT to decrease before initiating argatroban injection therapy (7.1).
- Warfarin: Concomitant use results in increased prolongation of PT and INR (7.2).
- Thrombolytic agents or glycoprotein IIb/IIIa antagonists: Safety and effectiveness of concomitant use with argatroban have not been established (7.4, 7.5).

8 USE IN SPECIFIC POPULATIONS

- Lactation: Discontinue nursing or drug, taking into account the importance of the drug to the mother (8.2).
- Pediatric Use: Safety and effectiveness have not been established (8.4).

FULL PRESCRIBING INFORMATION

1 INDICATIONS AND USAGE

1.1 Heparin-Induced Thrombocytopenia

Argatroban injection is indicated for prophylaxis or treatment of thrombosis in adult patients with heparin-induced thrombocytopenia (HIT).

1.2 Percutaneous Coronary Intervention

Argatroban injection is indicated as an anticoagulant in adult patients with or at risk for HIT undergoing percutaneous coronary intervention (PCI).

2 DOSAGE AND ADMINISTRATION

2.1 Preparation for Intravenous Administration

Argatroban injection 250 mg per 2.5 mL (100 mg per mL) must be diluted 100-fold prior to infusion. Argatroban injection should not be mixed with other drugs prior to dilution.
Prior to administration, argatroban injection should be diluted in 0.9% Sodium Chloride Injection, 5% Dextrose Injection, or Lactated Ringer’s Injection to a final concentration of 1 mg/mL. The contents of each 2.5 mL vial should be diluted 100-fold by mixing with 250 mL of diluent. Use 250 mg (2.5 mL) per 250 mL of diluent or 500 mg (5 mL) per 500 mL of diluent.

The constituted solution must be mixed by repeated inversion of the diluent bag for 1 minute. Upon preparation, the solution may show slight haziness due to the formation of microprecipitates that dissolve upon continued mixing. Ionic solutions such as 0.9% Sodium Chloride or Lactated Ringers may require a longer mixing time. Use of diluent at room temperature is recommended. The final solution must be clear before use. If the solution is cloudy, or if an insoluble precipitate is noted, the bag should be discarded. The pH of the intravenous solution prepared as recommended is 3.2 to 7.5.

Solutions prepared are physically, chemically, and microbiologically stable when stored as directed below in Table 1 and protected from light:

Table 1 Recommended Storage Conditions of Diluted Solution
Diluent | Storage Limit | Storage Temperature
0.9% Sodium Chloride Injection | 96 hours | 20 to 25°C (68 to 77°F)
0.9% Sodium Chloride Injection | 96 hours | 2 to 8°C (36 to 46°F)
5% Dextrose Injection or Lactated Ringer’s Injection | 4 hours | 20 to 25°C (68 to 77°F)
5% Dextrose Injection or Lactated Ringer’s Injection | 4 hours | 2 to 8°C (36 to 46°F)

Discard unused final product at the completion of these post dilution storage periods. Prepared solutions should not be exposed to direct sunlight. No significant potency losses have been noted following simulated delivery of the solution through intravenous tubing.

Parenteral drug products should be inspected visually for particulate matter and discoloration prior to administration whenever solution and container permit.

2.2 Dosing in Patients with Heparin-Induced Thrombocytopenia

Initial Dosage:

Before administering argatroban injection, discontinue heparin therapy and obtain a baseline aPTT. The recommended initial dose of argatroban injection for adult patients without hepatic impairment is 2 mcg/kg/min, administered as a continuous infusion (see Table 2).

Table 2 Recommended Doses and Infusion Rates for 2 mcg/kg/min Dose of Argatroban Injection for Patients with HIT* and Without Hepatic Impairment (1 mg/mL Final Concentration)
Body Weight (kg) | Dose (mcg/min) | Infusion Rate (mL/hr)
50 | 100 | 6
60 | 120 | 7
70 | 140 | 8
80 | 160 | 10
90 | 180 | 11
100 | 200 | 12
110 | 220 | 13
120 | 240 | 14
130 | 260 | 16
140 | 280 | 17

*with or without thrombosis

Monitoring Therapy:
For use in HIT, therapy with argatroban injection is monitored using the aPTT with a target range of 1.5 to 3 times the initial baseline value (not to exceed 100 seconds). Tests of anticoagulant effects (including the aPTT) typically attain steady-state levels within 1 to 3 hours following initiation of argatroban injection. Check the aPTT 2 hours after initiation of therapy and after any dose change to confirm that the patient has attained the desired therapeutic range.

Dosage Adjustment:
After the initiation of argatroban injection, adjust the dose (not to exceed 10 mcg/kg/min) as necessary to obtain a steady-state aPTT in the target range [see Clinical Studies (14.1)].

2.3 Dosing in Patients Undergoing Percutaneous Coronary Intervention

Initial Dosage:
Initiate an infusion of argatroban injection at 25 mcg/kg/min and administer a bolus of 350 mcg/kg via a large bore intravenous line over 3 to 5 minutes (see Table 3). Check an activated clotting time (ACT) 5 to 10 minutes after the bolus dose is completed. The PCI procedure may proceed if the ACT is greater than 300 seconds.

Dosage Adjustment:
If the ACT is less than 300 seconds, an additional intravenous bolus dose of 150 mcg/kg should be administered, the infusion dose increased to 30 mcg/kg/min, and the ACT checked 5 to 10 minutes later (see Table 3).

If the ACT is greater than 450 seconds, decrease the infusion rate to 15 mcg/kg/min, and check the ACT 5 to 10 minutes later (see Table 4).

Continue titrating the dose until a therapeutic ACT (between 300 and 450 seconds) has been achieved; continue the same infusion rate for the duration of the PCI procedure.

In case of dissection, impending abrupt closure, thrombus formation during the procedure, or inability to achieve or maintain an ACT over 300 seconds, additional bolus doses of 150 mcg/kg may be administered and the infusion dose increased to 40 mcg/kg/min. Check the ACT after each additional bolus or change in the rate of infusion.

Table 3 Recommended Starting and Maintenance Doses (Within the Target ACT Range) of Argatroban Injection in Patients Undergoing PCI Without Hepatic Impairment (1 mg/mL Final Concentration)
Body Weight (kg) | Starting Bolus Dose (350 mcg/kg) |  | Starting and Maintenance Continuous Infusion Dosing For ACT 300 to 450 seconds 25 mcg/kg/min
Body Weight (kg) | Bolus Dose (mcg) | Bolus Volume (mL) | Continuous Infusion Dose (mcg/min) | Continuous Infusion Rate (mL/hr)
50 | 17,500 | 18 | 1,250 | 75
60 | 21,000 | 21 | 1,500 | 90
70 | 24,500 | 25 | 1,750 | 105
80 | 28,000 | 28 | 2,000 | 120
90 | 31,500 | 32 | 2,250 | 135
100 | 35,000 | 35 | 2,500 | 150
110 | 38,500 | 39 | 2,750 | 165
120 | 42,000 | 42 | 3,000 | 180
130 | 45,500 | 46 | 3,250 | 195
140 | 49,000 | 49 | 3,500 | 210

NOTE: 1 mg = 1,000 mcg; 1 kg = 2.2 lbs

Table 4 Recommended Dose Adjustments of Argatroban Injection for Patients Outside of ACT Target Range Undergoing PCI Without Hepatic Impairment (1 mg/mL Final Concentration)
Body Weight (kg) | If ACT Less than 300 seconds Dosage Adjustment† 30 mcg/kg/min |  |  |  | If ACT Greater than 450 seconds Dosage Adjustment* 15 mcg/kg/min
Body Weight (kg) | Additional Bolus Dose (mcg) | Bolus Volume (mL) | Continuous Infusion Dose (mcg/min) | Continuous Infusion Rate (mL/hr) | Continuous Infusion Dose (mcg/min) | Continuous Infusion Rate (mL/hr)
50 | 7,500 | 8 | 1,500 | 90 | 750 | 45
60 | 9,000 | 9 | 1,800 | 108 | 900 | 54
70 | 10,500 | 11 | 2,100 | 126 | 1,050 | 63
80 | 12,000 | 12 | 2,400 | 144 | 1,200 | 72
90 | 13,500 | 14 | 2,700 | 162 | 1,350 | 81
100 | 15,000 | 15 | 3,000 | 180 | 1,500 | 90
110 | 16,500 | 17 | 3,300 | 198 | 1,650 | 99
120 | 18,000 | 18 | 3,600 | 216 | 1,800 | 108
130 | 19,500 | 20 | 3,900 | 234 | 1,950 | 117
140 | 21,000 | 21 | 4,200 | 252 | 2,100 | 126

NOTE: 1 mg = 1,000 mcg; 1 kg = 2.2 lbs

† Additional intravenous bolus dose of 150 mcg/kg should be administered if ACT less than 300 seconds.

* No bolus dose is given if ACT greater than 450 seconds

Monitoring Therapy:
For use in PCI, therapy with argatroban injection is monitored using ACT. Obtain ACTs before dosing, 5 to 10 minutes after bolus dosing, following adjustments in the infusion rate, and at the end of the PCI procedure. Obtain additional ACTs every 20 to 30 minutes during a prolonged procedure.
Continued Anticoagulation after PCI:
If a patient requires anticoagulation after the procedure, argatroban injection may be continued, but at a rate of 2 mcg/kg/min and adjusted as needed to maintain the aPTT in the desired range [see Dosage and Administration (2.1)].

2.4 Dosing in Patients with Hepatic Impairment

Initial Dosage:

For adult patients with HIT and moderate or severe hepatic impairment (based on Child-Pugh classification), an initial dose of 0.5 mcg/kg/min is recommended, based on the approximately 4-fold decrease in argatroban injection clearance relative to those with normal hepatic function. Monitor the aPTT closely, and adjust the dosage as clinically indicated.

Monitoring Therapy:
Achievement of steady-state aPTT levels may take longer and require more dose adjustments in patients with hepatic impairment compared to patients with normal hepatic function.

For patients with hepatic impairment undergoing PCI and who have HIT or are at risk for HIT, carefully titrate argatroban until the desired level of anticoagulation is achieved. Use of argatroban in PCI patients with clinically significant hepatic disease or AST/ALT levels greater than or equal to 3 times the upper limit of normal should be avoided [see Warnings and Precautions (5.2)].

2.5 Conversion to Oral Anticoagulant Therapy

Initiating Oral Anticoagulant Therapy:
When converting patients from argatroban injection to oral anticoagulant therapy, consider the potential for combined effects on INR with co-administration of argatroban and warfarin. A loading dose of warfarin should not be used. Initiate therapy using the expected daily dose of warfarin. To avoid prothrombotic effects and to ensure continuous anticoagulation when initiating warfarin, it is suggested that argatroban and warfarin therapy be overlapped. There are insufficient data available to recommend the duration of the overlap.

Co-Administration of Warfarin and Argatroban Injection at Doses up to 2 mcg/kg/min:
Measure INR daily while argatroban injection and warfarin are co-administered. In general, with doses of argatroban injection up to 2 mcg/kg/min, argatroban injection can be discontinued when the INR is greater than 4 on combined therapy. After argatroban injection is discontinued, repeat the INR measurement in 4 to 6 hours. If the repeat INR is below the desired therapeutic range, resume the infusion of argatroban injection and repeat the procedure daily until the desired therapeutic range on warfarin alone is reached.

Co-Administration of Warfarin and Argatroban Injection at Doses Greater than 2 mcg/kg/min:
For doses of argatroban injection greater than 2 mcg/kg/min, the relationship of INR between warfarin alone to the INR on warfarin plus argatroban injection is less predictable. In this case, in order to predict the INR on warfarin alone, temporarily reduce the dose of argatroban injection to a dose of 2 mcg/kg/min. Repeat the INR on argatroban injection and warfarin 4 to 6 hours after reduction of the argatroban injection dose and follow the process outlined above for administering argatroban injection at doses up to 2 mcg/kg/min.

3 DOSAGE FORMS AND STRENGTHS

Injection: 250 mg per 2.5 mL (100 mg per mL) clear solution in a single-dose vial.

4 CONTRAINDICATIONS

Argatroban is contraindicated in:

- Patients with major bleeding [see Warnings and Precautions (5.1)].
- Patients with a history of hypersensitivity to argatroban. Airway, skin, and generalized hypersensitivity reactions have been reported [see Adverse Reactions (6.4)].

5 WARNINGS AND PRECAUTIONS

5.1 Risk of Hemorrhage

Hemorrhage can occur at any site in the body in patients receiving argatroban. Unexplained fall in hematocrit or blood pressure may indicate hemorrhage. Intracranial and retroperitoneal hemorrhage have been reported [see Adverse Reactions (6.1, 6.2, and 6.3)]. The risk of hemorrhage with argatroban may be increased in severe hypertension, immediately following lumbar puncture, spinal anesthesia, major surgery (especially involving the brain, spinal cord, or eye), hematologic conditions associated with increased bleeding tendencies such as congenital or acquired bleeding disorders, and gastrointestinal lesions such as ulcerations.

Concomitant use of argatroban with antiplatelet agents, thrombolytics, and other anticoagulants may increase the risk of bleeding.

5.2 Use in Hepatic Impairment

When administering argatroban to patients with hepatic impairment, start with a lower dose and carefully titrate until the desired level of anticoagulation is achieved. Achievement of steady-state aPTT levels may take longer and require more argatroban dose adjustments in patients with hepatic impairment compared to patients with normal hepatic function [see Use in Specific Populations (8.6)]. Also, upon cessation of argatroban infusion in the hepatically impaired patient, full reversal of anticoagulant effects may require longer than 4 hours due to decreased clearance and increased elimination half-life of argatroban [see Dosage and Administration (2.3) and Clinical Pharmacology (12.3)]. Avoid the use of high doses of argatroban in patients undergoing PCI who have clinically significant hepatic disease or AST/ALT levels greater than or equal to 3 times the upper limit of normal.

5.3 Laboratory Tests

Anticoagulation effects associated with argatroban infusion at doses up to 40 mcg/kg/min correlate with increases of the activated partial thromboplastin time (aPTT). Although other global clot-based tests including prothrombin time (PT), the International Normalized Ratio (INR), and thrombin time (TT) are affected by argatroban, the therapeutic ranges for these tests have not been identified for argatroban therapy. In clinical trials in PCI, the activated clotting time (ACT) was used for monitoring argatroban anticoagulant activity during the procedure. The concomitant use of argatroban and warfarin results in prolongation of the PT and INR beyond that produced by warfarin alone [see Dosage and Administration (2.5) and Clinical Pharmacology (12.2)].

6 ADVERSE REACTIONS

The following adverse reaction is also discussed in other sections of the labeling:
• Risk of Hemorrhage [see Warnings and Precautions (5.1)].

6.1 Adverse Events in Patients with HIT (with or without Thrombosis)

Because clinical trials are conducted under widely varying conditions, adverse event rates observed in the clinical trials of a drug cannot be directly compared to rates in the clinical trials of another drug and may not reflect the rates observed in practice.
The following safety information is based on all 568 patients treated with argatroban in Study 1 and Study 2. The safety profile of the patients from these studies is compared with that of 193 historical controls in which the adverse events were collected retrospectively. Adverse events are separated into hemorrhagic and non-hemorrhagic events.

Major bleeding was defined as bleeding that was overt and associated with a hemoglobin decrease > 2 g/dL, that led to a transfusion of > 2 units, or that was intracranial, retroperitoneal, or into a major prosthetic joint. Minor bleeding was overt bleeding that did not meet the criteria for major bleeding.

Table 5 gives an overview of the most frequently observed hemorrhagic events, presented separately by major and minor bleeding, sorted by decreasing occurrence among argatroban-treated patients with HIT (with or without thrombosis).

Table 5 Major and Minor Hemorrhagic Adverse Events in Patients with HIT*
Major Hemorrhagic Eventsa
 | Argatroban-Treated Patients (Study 1 and Study 2) (n = 568) % | Historical Controlc (n = 193) %
Overall bleeding | 5.3 | 6.7
Gastrointestinal | 2.3 | 1.6
Genitourinary and hematuria | 0.9 | 0.5
Decrease in hemoglobin and hematocrit | 0.7 | 0
Multisystem hemorrhage and DIC | 0.5 | 1
Limb and BKA stump | 0.5 | 0
Intracranial hemorrhage | 0b | 0.5
Minor Hemorrhagic Eventsa
Gastrointestinal | 14.4 | 18.1
Genitourinary and hematuria | 11.6 | 0.8
Decrease in hemoglobin and hematocrit | 10.4 | 0
Groin | 5.4 | 3.1
Hemoptysis | 2.9 | 0.8
Brachial | 2.4 | 0.8

* with or without thrombosis

a Patients may have experienced more than 1 adverse event.

b One patient experienced intracranial hemorrhage 4 days after discontinuation of argatroban and following therapy with urokinase and oral anticoagulation.

c The historical control group consisted of patients with a clinical diagnosis of HIT (with or without thrombosis) that were considered eligible by an independent medical panel.

DIC = disseminated intravascular coagulation.

BKA = below-the-knee amputation.

Table 6 gives an overview of the most frequently observed non-hemorrhagic events sorted by decreasing frequency of occurrence (greater than or equal to 2%) among argatroban-treated HIT/HITTS patients.

Table 6 Non-hemorrhagic Adverse Events in Patientsa with HITb
 | Argatroban-Treated Patients (Study 1 and Study 2) (n = 568) % | Historical Controlc (n = 193) %
Dyspnea | 8.1 | 8.8
Hypotension | 7.2 | 2.6
Fever | 6.9 | 2.1
Diarrhea | 6.2 | 1.6
Sepsis | 6 | 12.4
Cardiac arrest | 5.8 | 3.1
Nausea | 4.8 | 0.5
Ventricular tachycardia | 4.8 | 3.1
Pain | 4.6 | 3.1
Urinary tract infection | 4.6 | 5.2
Vomiting | 4.2 | 0
Infection | 3.7 | 3.6
Pneumonia | 3.3 | 9.3
Atrial fibrillation | 3 | 11.4
Coughing | 2.8 | 1.6
Abnormal renal function | 2.8 | 4.7
Abdominal pain | 2.6 | 1.6
Cerebrovascular disorder | 2.3 | 4.1

a Patients may have experienced more than 1 adverse event.

b with or without thrombosis

c The historical control group consisted of patients with a clinical diagnosis of HIT (with or without thrombosis) that were considered eligible by an independent medical panel.

6.2 Adverse Events in Patients with or at Risk for HIT Patients Undergoing PCI

The following safety information is based on 91 patients initially treated with argatroban and 21 patients subsequently re-exposed to argatroban for a total of 112 PCIs with argatroban anticoagulation. Adverse events are separated into hemorrhagic (Table 7) and non-hemorrhagic (Table 8) events.

Major bleeding was defined as bleeding that was overt and associated with a hemoglobin decrease > 5 g/dL, that led to a transfusion of > 2 units, or that was intracranial, retroperitoneal, or into a major prosthetic joint. The rate of major bleeding events in patients treated with argatroban in the PCI trials was 1.8%.

Table 7 Major and Minor Hemorrhagic Adverse Events in Patients with HIT Undergoing PCI
Major Hemorrhagic Eventsa
 | Argatroban-Treated Patients (n = 112)b %
Retroperitoneal | 0.9
Gastrointestinal | 0.9
Intracranial | 0
Minor Hemorrhagic Eventsa
 | Argatroban-Treated Patients (n = 112)b %
Groin (bleeding or hematoma) | 3.6
Gastrointestinal (includes hematemesis) | 2.6
Genitourinary (includes hematuria) | 1.8
Decrease in hemoglobin and/or hematocrit | 1.8
CABG (coronary arteries) | 1.8
Access site | 0.9
Hemoptysis | 0.9
Other | 0.9

a Patients may have experienced more than 1 adverse event.

b 91 patients who underwent 112 interventions.

CABG = coronary artery bypass graft.

Table 8 gives an overview of the most frequently observed non-hemorrhagic events (greater than 2%), sorted by decreasing frequency of occurrence among argatroban-treated PCI patients.

Table 8 Non-hemorrhagic Adverse Eventsa in Patients with HIT Undergoing PCI
 | Argatroban Proceduresa (n = 112)b%
Chest pain | 15.2
Hypotension | 10.7
Back pain | 8
Nausea | 7.1
Vomiting | 6.3
Headache | 5.4
Bradycardia | 4.5
Abdominal pain | 3.6
Fever | 3.6
Myocardial infarction | 3.6

a Patients may have experienced more than 1 adverse event.

b 91 patients who underwent 112 interventions.

There were 22 serious adverse events in 17 PCI patients (19.6% in 112 interventions). Table 9 lists the serious adverse events occurring in argatroban-treated patients with or at risk for HIT undergoing PCI.

Table 9 Serious Adverse Events in Patients with HIT Undergoing PCIa
Coded Term | Argatroban Proceduresb (n = 112)
Myocardial infarction | 4 (3.5%)
Angina pectoris | 2 (1.8%)
Coronary thrombosis | 2 (1.8%)
Myocardial ischemia | 2 (1.8%)
Occlusion coronary | 2 (1.8%)
Chest pain | 1 (0.9%)
Fever | 1 (0.9%)
Retroperitoneal hemorrhage | 1 (0.9%)
Aortic stenosis | 1 (0.9%)
Arterial thrombosis | 1 (0.9%)
Gastrointestinal hemorrhage | 1 (0.9%)
Gastrointestinal disorder (GERD) | 1 (0.9%)
Cerebrovascular disorder | 1 (0.9%)
Lung edema | 1 (0.9%)
Vascular disorder | 1 (0.9%)

a Individual events may also have been reported elsewhere (see Table 7 and 8).

b 91 patients underwent 112 procedures. Some patients may have experienced more than 1 event.

6.3 Intracranial Bleeding in Other Populations

Increased risks for intracranial bleeding have been observed in investigational studies of argatroban for other uses. In a study of patients with acute myocardial infarction receiving both argatroban and thrombolytic therapy (streptokinase or tissue plasminogen activator), the overall frequency of intracranial bleeding was 1% (8 out of 810 patients). Intracranial bleeding was not observed in 317 subjects or patients who did not receive concomitant thrombolysis [see Drug Interactions (7.4)].

The safety and effectiveness of argatroban for cardiac indications other than PCI in patients with HIT have not been established. Intracranial bleeding was also observed in a prospective, placebo-controlled study of argatroban in patients who had onset of acute stroke within 12 hours of study entry. Symptomatic intracranial hemorrhage was reported in 5 of 117 patients (4.3%) who received argatroban at 1 to 3 mcg/kg/min and in none of the 54 patients who received placebo. Asymptomatic intracranial hemorrhage occurred in 5 (4.3%) and 2 (3.7%) of the patients, respectively.

6.4 Allergic Reactions

One hundred fifty-six allergic reactions or suspected allergic reactions were observed in 1,127 individuals who were treated with argatroban in clinical pharmacology studies or for various clinical indications. About 95% (148/156) of these reactions occurred in patients who concomitantly received thrombolytic therapy (e.g., streptokinase) or contrast media.

Allergic reactions or suspected allergic reactions in populations other than patients with HIT (with or without thrombosis) include (in descending order of frequency):

- Airway reactions (coughing, dyspnea): 10% or more
- Skin reactions (rash, bullous eruption): 1 to less than 10%
- General reactions (vasodilation): 1 to 10%

Limited data are available on the potential formation of drug-related antibodies. Plasma from 12 healthy volunteers treated with argatroban over 6 days showed no evidence of neutralizing antibodies. No loss of anticoagulant activity was noted with repeated administration of argatroban to more than 40 patients.

7 DRUG INTERACTIONS

7.1 Heparin

If argatroban is to be initiated after cessation of heparin therapy, allow sufficient time for heparin’s effect on the aPTT to decrease prior to initiation of argatroban therapy.

7.2 Oral Anticoagulant Agents

Pharmacokinetic drug-drug interactions between argatroban and warfarin (7.5 mg single oral dose) have not been demonstrated. However, the concomitant use of argatroban and warfarin (5 to 7.5 mg initial oral dose, followed by 2.5 to 6 mg/day orally for 6 to 10 days) results in prolongation of the prothrombin time (PT) and International Normalized Ratio (INR) [see Dosage and Administration (2.5) and Clinical Pharmacology (12.2)].

7.3 Aspirin/Acetaminophen

No drug-drug interactions have been demonstrated between argatroban and concomitantly administered aspirin or acetaminophen [see Clinical Pharmacology (12.3)].

7.4 Thrombolytic Agents

The safety and effectiveness of argatroban with thrombolytic agents have not been established [see Adverse Reactions (6.3)].

7.5 Glycoprotein IIb/IIIa Antagonists

The safety and effectiveness of argatroban with glycoprotein IIb/IIIa antagonists have not been established.

8 USE IN SPECIFIC POPULATIONS

8.1 Pregnancy

Risk Summary
Limited data from published literature and postmarketing reports do not suggest an association between argatroban and adverse fetal developmental outcomes. There are risks to the mother associated with untreated thrombosis in pregnancy and a risk of hemorrhage in the mother and fetus associated with use of anticoagulants (see Clinical Considerations). In animal reproductive studies, there was no evidence of adverse developmental outcomes with intravenous administration of argatroban during organogenesis in rats and rabbits at doses up to 0.3- and 0.2-times, respectively, the maximum recommended human dose (MHRD) (see Data).
The estimated background risk of major birth defects and miscarriage for the indicated population is unknown. All pregnancies have a background risk of birth defect, loss, or other adverse outcomes. In the U.S. general population, the estimated background risk of major birth defects and miscarriage in clinically recognized pregnancies is 2%-4% and 15%-20%, respectively.

Clinical Considerations
Disease-Associated Maternal and/or Embryo/Fetal Risk
Pregnancy confers an increased risk for thromboembolism that is higher for women with underlying thromboembolic disease and certain high risk pregnancy conditions. Published data describe that women with a previous history of venous thrombosis are at high risk for recurrence during pregnancy.
Fetal/Neonatal Adverse Reactions
Use of anticoagulants, including argatroban, may increase the risk of bleeding in the fetus and neonate. Monitor neonates for bleeding [see Warnings and Precautions (5.1, 5.3)].

Labor or Delivery
All patients receiving anticoagulants, including pregnant women, are at risk for bleeding. Pregnant women receiving argatroban should be carefully monitored for evidence of excessive bleeding or unexpected changes in coagulation parameters [see Warnings and Precautions (5.1, 5.3)].

Data
Animal data
Developmental studies performed in rats (during gestation Days 7 to 17) with argatroban at intravenous doses up to 27 mg/kg/day (0.3 times the maximum recommended human dose, based on body surface area) and in rabbits (during gestation Days 6 to 18) at intravenous doses up to 10.8 mg/kg/day (0.2 times the maximum recommended human dose, based on body surface area) have revealed no evidence of harm to the fetus.

8.2 Lactation

Risk Summary
There are no data on the presence of argatroban in human milk, or its effects on milk production. Argatroban is present in rat milk. The developmental and health benefits of breastfeeding should be considered along with the mother’s clinical need for Argatroban and any potential adverse effects on the breastfed infant from Argatroban or from the underlying maternal condition.
Data
Argatroban is detected in rat milk.

8.4 Pediatric Use

Safety and effectiveness have not been established in pediatric patients.

Argatroban was studied among 18 seriously ill pediatric patients who required an alternative to heparin anticoagulation. Most patients were diagnosed with HIT or suspected HIT. Age ranges of patients were less than 6 months, n = 8; six months to less than 8 years, n = 6; 8 to 16 years, n = 4. All patients had serious underlying conditions and were receiving multiple concomitant medications. Thirteen patients received argatroban solely as a continuous infusion (no bolus dose). Dosing was initiated in the majority of these 13 patients at 1 mcg/kg/min. Dosing was titrated as needed to achieve and maintain an aPTT of 1.5 to 3 times the baseline value. Most patients required multiple dose adjustments to maintain anticoagulation parameters within the desired range. During the 30-day study period, thrombotic events occurred during argatroban administration to two patients: and following argatroban discontinuation in three other patients. Major bleeding occurred among two patients: one patient experienced an intracranial hemorrhage after 4 days of argatroban therapy in the setting of sepsis and thrombocytopenia and another patient experienced an intracranial hemorrhage after receiving argatroban for greater than 14 days. The study findings did not establish the safe and effective use of argatroban in pediatric patients and the dosing of 1 mcg/kg/min was not supported by the pharmacokinetic data described below.
Pediatric Pharmacokinetics (PK) and Pharmacodynamics (PD)
PK parameters of argatroban were characterized in population PK/PD analysis model with sparse data from 15 seriously ill pediatric patients. Argatroban clearance in these seriously ill pediatric patients (0.16 L/hr/kg) was 50% lower compared to argatroban clearance in healthy adults (0.31 L/hr/kg). Four pediatric patients with elevated bilirubin (secondary to cardiac complications or hepatic impairment) had, on average, 80% lower clearance (0.03 L/hr/kg) when compared to pediatric patients with normal bilirubin levels.

These PK/PD analysis models based on a goal of aPTT prolongation of 1.5 to 3 times the baseline value and avoidance of an aPTT>100 seconds for seriously ill pediatric patients with HIT/HITTS who require an alternative to heparin suggested the following:

- For patients with normal hepatic function, a starting infusion rate of 0.75 mcg/kg/min may have comparable aPTT responses as a starting dose of 2 mcg/kg/min in healthy adults. Additionally, based on an evaluation of aPTT every two hours, increasing the dosage by 0.1 to 0.25 mcg/kg/min could achieve additional aPTT responses.
- For patients with hepatic impairment a starting infusion rate of 0.2 mcg/kg/min with increasing dosing by increments of 0.05 mcg/kg/min may have comparable argatroban exposure as expected with adult doses.

The safety and effectiveness of argatroban with the above dosing have not been adequately assessed in pediatric patients and the safety and effectiveness of argatroban is not established in pediatric patients. In addition, the described dosage did not take into account multiple factors that could affect the dosage such as current aPTT, target aPTT, and the clinical status of the patient.

8.5 Geriatric Use

Of the total number of subjects (1,340) in clinical studies of argatroban, 35% were 65 and over. In the clinical studies of adult patients with HIT (with or without thrombosis), the effectiveness of argatroban was not affected by age. No trends were observed across age groups for both aPTT and the ACT. The safety analysis did suggest that older patients had increased underlying conditions, which may predispose them to events. The studies were not sized appropriately to detect differences in safety between age groups.

8.6 Hepatic Impairment

Dose reduction and careful titration are required when administering argatroban to patients with hepatic impairment. Reversal of anticoagulation effect may be prolonged in this population [see Dosage and Administration (2.3), Warnings and Precautions (5.2), Clinical Pharmacology (12.3)].

10 OVERDOSAGE

Excessive anticoagulation, with or without bleeding, may be controlled by discontinuing argatroban or by decreasing the argatroban dose. In clinical studies, anticoagulation parameters generally returned from therapeutic levels to baseline within 2 to 4 hours after discontinuation of the drug. Reversal of anticoagulant effect may take longer in patients with hepatic impairment.

No specific antidote to argatroban is available; if life-threatening bleeding occurs and excessive plasma levels of argatroban are suspected, discontinue argatroban immediately and measure aPTT and other coagulation parameters. When argatroban was administered as a continuous infusion (2 mcg/kg/min) prior to and during a 4-hour hemodialysis session, approximately 20% of argatroban was cleared through dialysis.

Single intravenous doses of argatroban at 200, 124, 150, and 200 mg/kg were lethal to mice, rats, rabbits, and dogs, respectively. The symptoms of acute toxicity were loss of righting reflex, tremors, clonic convulsions, paralysis of hind limbs, and coma.

11 DESCRIPTION

Argatroban is a synthetic direct thrombin inhibitor and the chemical name is 1-[5-[(aminoiminomethyl)amino]-1-oxo-2-[[(1,2,3,4-tetrahydro-3-methyl-8-quinolinyl)sulfonyl]amino]pentyl]-4-methyl-2-piperidinecarboxylic acid, monohydrate. Argatroban has 4 asymmetric carbons. One of the asymmetric carbons has an R configuration (stereoisomer Type I) and an S configuration (stereoi-somer Type II). Argatroban consists of a mixture of R and S stereoisomers at a ratio of approximately 65:35.

The molecular formula of argatroban is C23H36N6O5S•H2O. Its molecular weight is 526.66 g/mol. The structural formula is:

Argatroban is a white, odorless crystalline powder that is freely soluble in glacial acetic acid, slightly soluble in ethanol, and insoluble in acetone, ethyl acetate, and ether.

Argatroban injection is a sterile clear, colorless to pale yellow, slightly viscous solution in a single-dose amber vial containing 250 mg per 2.5 mL of argatroban. It is supplied as a solution intended for dilution prior to intravenous use. Each mL of sterile, nonpyrogenic solution contains 100 mg argatroban and 954 mg propylene glycol.

12 CLINICAL PHARMACOLOGY

12.1 Mechanism of Action

Argatroban is a direct thrombin inhibitor that reversibly binds to the thrombin active site. Argatroban does not require the co-factor antithrombin III for antithrombotic activity. Argatroban exerts its anticoagulant effects by inhibiting thrombin-catalyzed or -induced reactions, including fibrin formation; activation of coagulation factors V, VIII, and XIII; activation of protein C; and platelet aggregation.

Argatroban inhibits thrombin with an inhibition constant (Ki) of 0.04 µM. At therapeutic concentrations, argatroban has little or no effect on related serine proteases (trypsin, factor Xa, plasmin, and kallikrein).

Argatroban is capable of inhibiting the action of both free and clot-associated thrombin.

12.2 Pharmacodynamics

When argatroban is administered by continuous infusion, anticoagulant effects and plasma concentrations of argatroban follow similar, predictable temporal response profiles, with low intersubject variability. Immediately upon initiation of argatroban infusion, anticoagulant effects are produced as plasma argatroban concentrations begin to rise. Steady-state levels of both drug and anticoagulant effect are typically attained within 1 to 3 hours and are maintained until the infusion is discontinued or the dosage adjusted. Steady-state plasma argatroban concentrations increase proportionally with dose (for infusion doses up to 40 mcg/kg/min in healthy subjects) and are well correlated with steady-state anticoagulant effects. For infusion doses up to 40 mcg/kg/min, argatroban increases in a dose-dependent fashion, the activated partial thromboplastin time (aPTT), the activated clotting time (ACT), the prothrombin time (PT), the International Normalized Ratio (INR), and the thrombin time (TT) in healthy volunteers and cardiac patients. Representative steady-state plasma argatroban concentrations and anticoagulant effects are shown below for argatroban infusion doses up to 10 mcg/kg/min (see Figure 1).

Figure 1 Relationship at Steady-State Between Argatroban Dose, Plasma Argatroban Concentration and Anticoagulant Effect

Effect on International Normalized Ratio (INR):

Because argatroban is a direct thrombin inhibitor, co-administration of argatroban and warfarin produces a combined effect on the laboratory measurement of the INR. However, concurrent therapy, compared to warfarin monotherapy, exerts no additional effect on vitamin K–dependent factor Xa activity.
The relationship between INR on co-therapy and warfarin alone is dependent on both the dose of argatroban and the thromboplastin reagent used. This relationship is influenced by the International Sensitivity Index (ISI) of the thromboplastin. Data for 2 commonly utilized thromboplastins with ISI values of 0.88 (Innovin, Dade) and 1.78 (Thromboplastin C Plus, Dade) are presented in Figure 2 for an argatroban dose of 2 mcg/kg/min. Thromboplastins with higher ISI values than shown result in higher INRs on combined therapy of warfarin and argatroban. These data are based on results obtained in normal individuals [see Drug Interactions (7.2), Dosage and Administration (2.5)].

Figure 2 INR Relationship of Argatroban Plus Warfarin Versus Warfarin Alone

Figure 2 demonstrates the relationship between INR for warfarin alone and INR for warfarin co-administered with argatroban at a dose of 2 mcg/kg/min. To calculate INR for warfarin alone (INRW), based on INR for co-therapy of warfarin and argatroban (INRWA), when the argatroban dose is 2 mcg/kg/min, use the equation next to the appropriate curve. Example: At a dose of 2 mcg/kg/min and an INR performed with Thromboplastin A, the equation 0.19 + 0.57 (INRWA) = INRW would allow a prediction of the INR on warfarin alone (INRW). Thus, using an INRWA value of 4 obtained on combined therapy: INRW = 0.19 + 0.57 (4) = 2.47 as the value for INR on warfarin alone. The error (confidence interval) associated with a prediction is ± 0.4 units. Similar linear relationships and prediction errors exist for argatroban at a dose of 1 mcg/kg/min. Thus, for argatroban doses of 1 or 2 mcg/kg/min, INRW can be predicted from INRWA. For argatroban doses greater than 2 mcg/kg/min, the error associated with predicting INRW from INRWA is ± 1. Thus, INRW cannot be reliably predicted from INRWA at doses greater than 2 mcg/kg/min.

12.3 Pharmacokinetics

Distribution:

Argatroban distributes mainly in the extra cellular fluid as evidenced by an apparent steady-state volume of distribution of 174 mL/kg (12.18 L in a 70 kg adult). Argatroban is 54% bound to human serum proteins, with binding to albumin and α1-acid glycoprotein being 20% and 34%, respectively.

Metabolism:

The main route of argatroban metabolism is hydroxylation and aromatization of the 3-methyltetrahydroquinoline ring in the liver. The formation of each of the 4 known metabolites is catalyzed in vitro by the human liver microsomal cytochrome P450 enzymes CYP3A4/5. The primary metabolite (M1) exerts 3- to 5-fold weaker anticoagulant effects than argatroban. Unchanged argatroban is the major component in plasma. The plasma concentrations of M1 range between 0% and 20% of that of the parent drug. The other metabolites (M2 to M4) are found only in very low quantities in the urine and have not been detected in plasma or feces. These data, together with the lack of effect of erythromycin (a potent CYP3A4/5 inhibitor) on argatroban pharmacokinetics, suggest that CYP3A4/5-mediated metabolism is not an important elimination pathway in vivo.

Total body clearance is approximately 5.1 mL/kg/min (0.31 L/kg/hr) for infusion doses up to 40 mcg/kg/min. The terminal elimination half-life of argatroban ranges between 39 and 51 minutes.

There is no interconversion of the 21–(R):21–(S) diastereoisomers. The plasma ratio of these diastereoisomers is unchanged by metabolism or hepatic impairment, remaining constant at 65:35 (± 2%).

Excretion:

Argatroban is excreted primarily in the feces, presumably through biliary secretion. In a study in which ^14C-argatroban (5 mcg/kg/min) was infused for 4 hours into healthy subjects, approximately 65% of the radioactivity was recovered in the feces within 6 days of the start of infusion with little or no radioactivity subsequently detected. Approximately 22% of the radioactivity appeared in the urine within 12 hours of the start of infusion. Little or no additional urinary radioactivity was subsequently detected. Average percent recovery of unchanged drug, relative to total dose, was 16% in urine and at least 14% in feces.

Special Populations:

Hepatic Impairment:

The dosage of argatroban should be decreased in patients with hepatic impairment [see Dosage and Administration (2.3) and Warnings and Precautions (5.2)]. Patients with hepatic impairment were not studied in percutaneous coronary intervention (PCI) trials. At a dose of 2.5 mcg/kg/min, hepatic impairment is associated with decreased clearance and increased elimination half-life of argatroban (to 1.9 mL/kg/min and 181 minutes, respectively, for patients with a Child-Pugh score greater than 6).
Renal Impairment:

No dosage adjustment is necessary in patients with renal dysfunction. The effect of renal disease on the pharmacokinetics of argatroban was studied in 6 subjects with normal renal function (mean Clcr = 95 ± 16 mL/min) and in 18 subjects with mild (mean Clcr = 64 ± 10 mL/min), moderate (mean Clcr = 41 ± 5.8 mL/min), and severe (mean Clcr = 5 ± 7 mL/min) renal impairment. The pharmacokinetics and pharmacodynamics of argatroban at dosages up to 5 mcg/kg/min were not significantly affected by renal dysfunction.

Use of argatroban was evaluated in a study of 12 patients with stable end-stage renal disease undergoing chronic intermittent hemodialysis. Argatroban was administered at a rate of 2 to 3 mcg/kg/min (begun at least 4 hours prior to dialysis) or as a bolus dose of 250 mcg/kg at the start of dialysis followed by a continuous infusion of 2 mcg/kg/min. Although these regimens did not achieve the goal of maintaining ACT values at 1.8 times the baseline value throughout most of the hemodialysis period, the hemodialysis sessions were successfully completed with both of these regimens. The mean ACTs produced in this study ranged from 1.39 to 1.82 times baseline, and the mean aPTTs ranged from 1.96 to 3.4 times baseline. When argatroban was administered as a continuous infusion of 2 mcg/kg/min prior to and during a 4-hour hemodialysis session, approximately 20% was cleared through dialysis.

Age, Gender:

There are no clinically significant effects of age or gender on the pharmacokinetics or pharmacodynamics (e.g., aPTT) of argatroban in adults.

Drug-Drug Interactions:

Digoxin:

In 12 healthy volunteers, intravenous infusion of argatroban (2 mcg/kg/min) over 5 days (study days 11 to 15) did not affect the steady-state pharmacokinetics of oral digoxin (0.375 mg daily for 15 days).

Erythromycin:

In 10 healthy subjects, orally administered erythromycin (a potent inhibitor of CYP3A4/5) at 500 mg four times daily for 7 days had no effect on the pharmacokinetics of argatroban at a dose of 1 mcg/kg/min for 5 hours. These data suggest oxidative metabolism by CYP3A4/5 is not an important elimination pathway in vivo for argatroban.

Aspirin and Acetaminophen:

Drug-drug interactions have not been demonstrated between argatroban and concomitantly administered aspirin (162.5 mg orally given 26 and 2 hours prior to initiation of argatroban 1 mcg/kg/min over 4 hours) or acetaminophen (1,000 mg orally given 12, 6, and 0 hours prior to, and 6 and 12 hours subsequent to, initiation of argatroban 1.5 mcg/kg/min over 18 hours).

13 NONCLINICAL TOXICOLOGY

13.1 Carcinogenesis, Mutagenesis, Impairment of Fertility

Carcinogenicity studies with argatroban have not been performed.

Argatroban was not genotoxic in the Ames test, the Chinese hamster ovary cell (CHO/HGPRT) forward mutation test, the Chinese hamster lung fibroblast chromosome aberration test, the rat hepatocyte, and WI-38 human fetal lung cell unscheduled DNA synthesis (UDS) tests, or the mouse micronucleus test.

Argatroban at intravenous doses up to 27 mg/kg/day (0.3 times the recommended maximum human dose based on body surface area) had no effect on fertility and reproductive function of male and female rats.

14 CLINICAL STUDIES

14.1 Heparin-Induced Thrombocytopenia

The safety and efficacy of argatroban were evaluated in a historically controlled efficacy and safety study (Study 1) and a follow-on efficacy and safety study (Study 2). These studies were comparable with regard to study design, study objectives, dosing regimens as well as study outline, conduct, and monitoring. In these studies, 568 adult patients were treated with argatroban and 193 adult patients made up the historical control group. Patients had a clinical diagnosis of heparin-induced thrombocytopenia, either without thrombosis (HIT) or with thrombosis (HITTS [heparin-induced thrombocytopenia and thrombosis syndrome]) and were males or non-pregnant females between the age of 18 and 80 years old. HIT/HITTS was defined by a fall in platelet count to less than 100,000/μL or a 50% decrease in platelets after the initiation of heparin therapy with no apparent explanation other than HIT. Patients with HITTS also had an arterial or venous thrombosis documented by appropriate imaging techniques or supported by clinical evidence such as acute myocardial infarction, stroke, pulmonary embolism, or other clinical indications of vascular occlusion. Patients who had documented histories of positive heparin-dependent antibody tests without current thrombocytopenia or heparin challenge (e.g., patients with latent disease) were also included if they required anticoagulation.

These studies did not include patients with documented unexplained aPTT greater than 200% of control at baseline, documented coagulation disorder or bleeding diathesis unrelated to HIT, a lumbar puncture within the past 7 days or a history of previous aneurysm, hemorrhagic stroke, or a thrombotic stroke within the past 6 months unrelated to HIT.

The initial dose of argatroban was 2 mcg/kg/min. Two hours after the start of the argatroban infusion, an aPTT level was obtained and dose adjustments were made (up to a maximum of 10 mcg/kg/min) to achieve a steady-state aPTT value that was 1.5 to 3 times the baseline value, not to exceed 100 seconds. Overall the mean aPTT level for HIT and HITTS patients during the argatroban infusion increased from baseline values of 34 and 38 seconds, respectively, to 62.5 and 64.5 seconds, respectively.

The primary efficacy analysis was based on a comparison of event rates for a composite endpoint that included death (all causes), amputation (all causes) or new thrombosis during the treatment and follow-up period (study days 0 to 37). Secondary analyses included evaluation of the event rates for the components of the composite endpoint as well as time-to-event analyses.

In Study 1, a total of 304 patients were enrolled as follows: active HIT (n = 129), active HITTS (n = 144), or latent disease (n = 31). Among the 193 historical controls, 139 (72%) had active HIT, 46 (24%) had active HITTS, and 8 (4%) had latent disease. Within each group, those with active HIT and those with latent disease were analyzed together. Positive laboratory confirmation of HIT/HITTS by the heparin-induced platelet aggregation test or serotonin release assay was demonstrated in 174 of 304 (57%) argatroban-treated patients (i.e., in 80 with HIT or latent disease and 94 with HITTS) and in 149 of 193 (77%) historical controls (i.e., in 119 with HIT or latent disease and 30 with HITTS). The test results for the remainder of the patients and controls were either negative or not determined.

There was a significant improvement in the composite outcome in patients with HIT and HITTS treated with argatroban versus those in the historical control group (see Table 10). The components of the composite endpoint are shown in Table 10.

Table 10 Efficacy Results of Study 1: Composite Endpointa and Individual Components, Ranked by Severityb
 | HIT |  | HITTS |  | HIT/HITTS
Parameter, N (%) | Control n = 147 | Argatroban n = 160 | Control n = 46 | Argatroban n = 144 | Control n = 193 | Argatroban n = 304
Composite Endpoint | 57 (38.8) | 41 (25.6) | 26 (56.5) | 63 (43.8) | 83 (43) | 104 (34.2)
Individual Componentsb:
Death | 32 (21.8) | 27 (16.9) | 13 (28.3) | 26 (18.1) | 45 (23.3) | 53 (17.4)
Amputation | 3 (2) | 3 (1.9) | 4 (8.7) | 16 (11.1) | 7 (3.6) | 19 (6.2)
New Thrombosis | 22 (15) | 11 (6.9) | 9 (19.6) | 21 (14.6) | 31 (16.1) | 32 (10.5)

a Death (all causes), amputation (all causes), or new thrombosis within 37-day study period.

b Reported as the most severe outcome among the components of composite endpoint (severity ranking: death > amputation > new thrombosis); patients may have had multiple outcomes.

Time-to-event analyses showed significant improvements in the time-to-first event in patients with HIT or HITTS treated with argatroban versus those in the historical control group. The between-group differences in the proportion of patients who remained free of death, amputation, or new thrombosis were statistically significant in favor of argatroban by these analyses.

A time-to-event analysis for the composite endpoint is shown in Figure 3 for patients with HIT and Figure 4 for patients with HITTS.

Figure 3 Time-to-First Event for the Composite Efficacy Endpoint: HIT Patients

STUDY 1

*Censored indicates no clinical endpoint (defined as death, amputation, or new thrombosis) was observed during the follow-up period (maximum period of follow-up was 37 days).

Figure 4 Time-to-First Event for the Composite Efficacy Endpoint: HITTS Patients

STUDY 1

*Censored indicates no clinical endpoint (defined as death, amputation, or new thrombosis) was observed during the follow-up period (maximum period of follow-up was 37 days).

In Study 2, a total of 264 patients were enrolled as follows: HIT (n = 125) or HITTS (n = 139). There was a significant improvement in the composite efficacy outcome for argatroban-treated patients, versus the same historical control group from Study 1, among patients having HIT (25.6% vs. 38.8%), patients having HITTS (41% vs. 56.5%), and patients having either HIT or HITTS (33.7% vs. 43%). Time-to-event analyses showed significant improvements in the time-to-first event in patients with HIT or HITTS treated with argatroban versus those in the historical control group. The between-group differences in the proportion of patients who remained free of death, amputation, or new thrombosis were statistically significant in favor of argatroban.

Anticoagulant Effect:
In Study 1, the mean (± SE) dose of argatroban administered was 2 ± 0.1 mcg/kg/min in the HIT arm and 1.9 ± 0.1 mcg/kg/min in the HITTS arm. Seventy-six percent of patients with HIT and 81% of patients with HITTS achieved a target aPTT at least 1.5-fold greater than the baseline aPTT at the first assessment occurring on average at 4.6 hours (HIT) and 3.9 hours (HITTS) following initiation of argatroban therapy.

No enhancement of aPTT response was observed in subjects receiving repeated administration of argatroban.

Platelet Count Recovery:

In Study 1, 53% of patients with HIT and 58% of patients with HITTS, had a recovery of platelet count by Day 3. Platelet Count Recovery was defined as an increase in platelet count to greater than 100,000/μL or to at least 1.5-fold greater than the baseline count (platelet count at study initiation) by Day 3 of the study.

14.2 Percutaneous Coronary Intervention (PCI) Patients with or at Risk for HIT

In 3 similarly designed trials, argatroban was administered to 91 patients with current or previous clinical diagnosis of HIT or heparin-dependent antibodies, who underwent a total of 112 percutaneous coronary interventions (PCIs) including percutaneous transluminal coronary angioplasty (PTCA), coronary stent placement, or atherectomy. Among the 91 patients undergoing their first PCI with argatroban, notable ongoing or recent medical history included myocardial infarction (n = 35), unstable angina (n = 23), and chronic angina (n = 34). There were 33 females and 58 males. The average age was 67.6 years (median 70.7, range 44 to 86), and the average weight was 82.5 kg (median 81 kg, range 49 to 141).

Twenty-one of the 91 patients had a repeat PCI using argatroban an average of 150 days after their initial PCI. Seven of 91 patients received glycoprotein IIb/IIIa inhibitors. Safety and efficacy were assessed against historical control populations who had been anticoagulated with heparin.

All patients received oral aspirin (325 mg) 2 to 24 hours prior to the interventional procedure. After venous or arterial sheaths were in place, anticoagulation was initiated with a bolus of argatroban of 350 mcg/kg via a large-bore intravenous line or through the venous sheath over 3 to 5 minutes. Simultaneously, a maintenance infusion of 25 mcg/kg/min was initiated to achieve a therapeutic activated clotting time (ACT) of 300 to 450 seconds. If necessary to achieve this therapeutic range, the maintenance infusion dose was titrated (15 to 40 mcg/kg/min) and/or an additional bolus dose of 150 mcg/kg could be given. Each patient’s ACT was checked 5 to 10 minutes following the bolus dose. The ACT was checked as clinically indicated. Arterial and venous sheaths were removed no sooner than 2 hours after discontinuation of argatroban and when the ACT was less than 160 seconds.

If a patient required anticoagulation after the procedure, argatroban could be continued, but at a lower infusion dose between 2.5 and 5 mcg/kg/min. An aPTT was drawn 2 hours after this dose reduction and the dose of argatroban then was adjusted as clinically indicated (not to exceed 10 mcg/kg/min), to reach an aPTT between 1.5 and 3 times baseline value (not to exceed 100 seconds).

In 92 of the 112 interventions (82%), the patient received the initial bolus of 350 mcg/kg and an initial infusion dose of 25 mcg/kg/min. The majority of patients did not require additional bolus dosing during the PCI procedure. The mean value for the initial ACT measurement after the start of dosing for all interventions was 379 sec (median 338 sec; 5th percentile-95th percentile 238 to 675 sec). The mean ACT value per intervention over all measurements taken during the procedure was 416 sec (median 390 sec; 5th percentile-95th percentile 261 to 698 sec). About 65% of patients had ACTs within the recommended range of 300 to 450 seconds throughout the procedure. The investigators did not achieve anticoagulation within the recommended range in about 23% of patients. However, in this small sample, patients with ACTs below 300 seconds did not have more coronary thrombotic events, and patients with ACTs over 450 seconds did not have higher bleeding rates.

Acute procedural success was defined as lack of death, emergent coronary artery bypass graft (CABG), or Q-wave myocardial infarction. Acute procedural success was reported in 98.2% of patients who underwent PCIs with argatroban anticoagulation compared with 94.3% of historical control patients anticoagulated with heparin (p = NS). Among the 112 interventions, 2 patients had emergency CABGs, 3 had repeat PTCAs, 4 had non-Q-wave myocardial infarctions, 3 had myocardial ischemia, 1 had an abrupt closure, and 1 had an impending closure (some patients may have experienced more than 1 event). No patients died.

16 HOW SUPPLIED/STORAGE AND HANDLING

NDC 63323-526-03, 250 mg per 2.5 mL (100 mg per mL) single-dose vial, packaged individually.
Storage

Store the vial in original carton at 20° to 25°C (68° to 77°F) [see USP Controlled Room Temperature]. Protect from freezing. Protect from light (keep in outer carton). If the solution is cloudy, or if an insoluble precipitate is noted, the vial should be discarded.

The container closure is not made with natural rubber latex.

17 PATIENT COUNSELING INFORMATION

Inform patients of the risks associated with Argatroban Injection as well as the plan for regular monitoring during administration of the drug [see Warnings and Precautions (5.1)].
Specifically, inform patients to report:

- the use of any other products known to affect bleeding.
- any medical history that may increase the risk for bleeding, including a history of severe hypertension; recent lumbar puncture or spinal anesthesia; major surgery, especially involving the brain, spinal cord, or eye; hematologic conditions associated with increased bleeding tendencies such as congenital or acquired bleeding disorders and gastrointestinal lesions such as ulcerations.
- any bleeding signs or symptoms.
- the occurrence of any signs or symptoms of allergic reactions (e.g., airway reactions, skin reactions and vasodilation reactions).

Manufactured by:
Lake Zurich, IL 60047
www.fresenius-kabi.com/us

451160H

PACKAGE LABEL

PACKAGE LABEL - PRINCIPAL DISPLAY - Argatroban 2.5 mL Single Dose Vial Label
Argatroban Injection
250 mg per 2.5 mL
(100 mg per mL)
For intravenous use only.
Must be diluted prior to administration.
Preservative free.
Single Dose Vial Rx only
Discard unused portion.

PACKAGE LABEL - PRINCIPAL DISPLAY - Argatroban 2.5 mL Single Dose Vial Carton Panel
Argatroban Injection
250 mg per 2.5 mL
(100 mg per mL)
For intravenous use only.
Must be diluted prior to administration.
Preservative free.
Sterile, Nonpyrogenic.
Discard unused portion.
Packaged Individually.
Rx only
Single Dose Vial